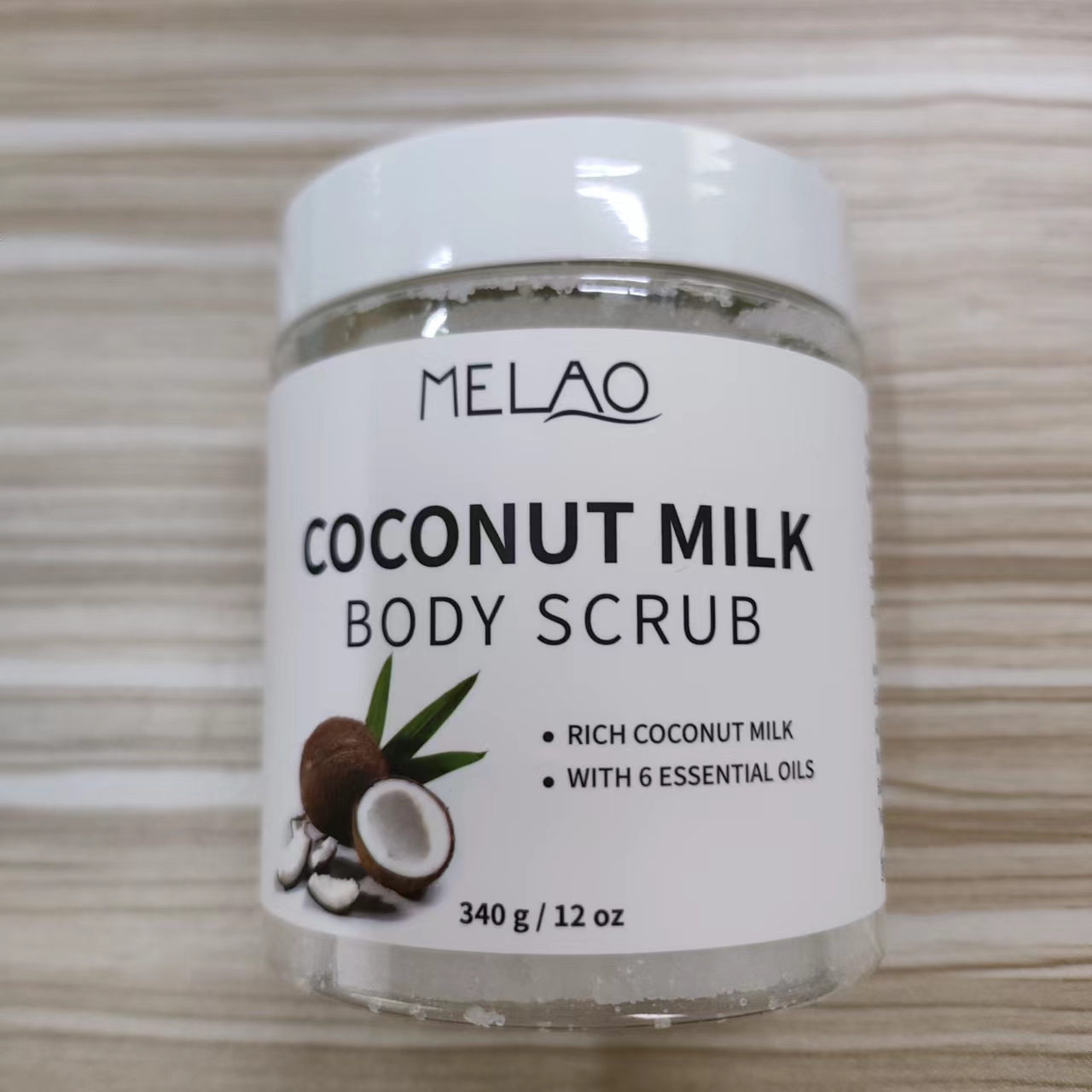 DRUG LABEL: MELAO COCONUT MILK BODY SCRUB
NDC: 74458-017 | Form: GRANULE
Manufacturer: Guangzhou Yilong Cosmetics Co., Ltd
Category: otc | Type: HUMAN OTC DRUG LABEL
Date: 20241122

ACTIVE INGREDIENTS: TOCOPHEROL 1 g/100 g; COCOS NUCIFERA (COCONUT) FRUIT EXTRACT 40 g/100 g
INACTIVE INGREDIENTS: VITIS VINIFERA (GRAPE) SEED OIL; PRUNUS ARMENIACA (APRICOT) FRUIT; SODIUM CHLORIDE; PRUNUS AMYGDALUS DULCIS (SWEET ALMOND) OIL; CARTHAMUS TINCTORIUS (SAFFLOWER) SEED OIL; HELIANTHUS ANNUUS (SUNFLOWER) SEED OIL; SEA SALT; PERSEA GRATISSIMA (AVOCADO) OIL

MELAO COCONUT MILK BODY SCRUB

DOSAGE AND ADMINISTRATION

Oily skin: once every two weeks.
Normal as well as dry skin: once a month.

INACTIVE INGREDIENT

Sodium Chloride

Prunus Amygdalus Dulcis (Sweet Almond) Oil

Carthamus Tinctorius (Safflower) Seed Oil

Helianthus Annuus (Sunflower) Seed Oil

Vitis Vinifera (Grape) Seed Oil

Prunus Armeniaca (Apricot) Kernel Oil

Persea Gratissima (Avocado) Oil

Maris Sal

PURPOSE

Exfoliating

WARNINGS

For external use only.

Stop use and ask a doctor if rash occurs.

Do not use on damaged or broken skin.

When using this product keep out of eyes. Rinse with water to remove.

Keep out of reach of children. If swallowed, get medical help or contact a Poison Control Center right away.